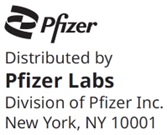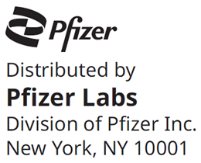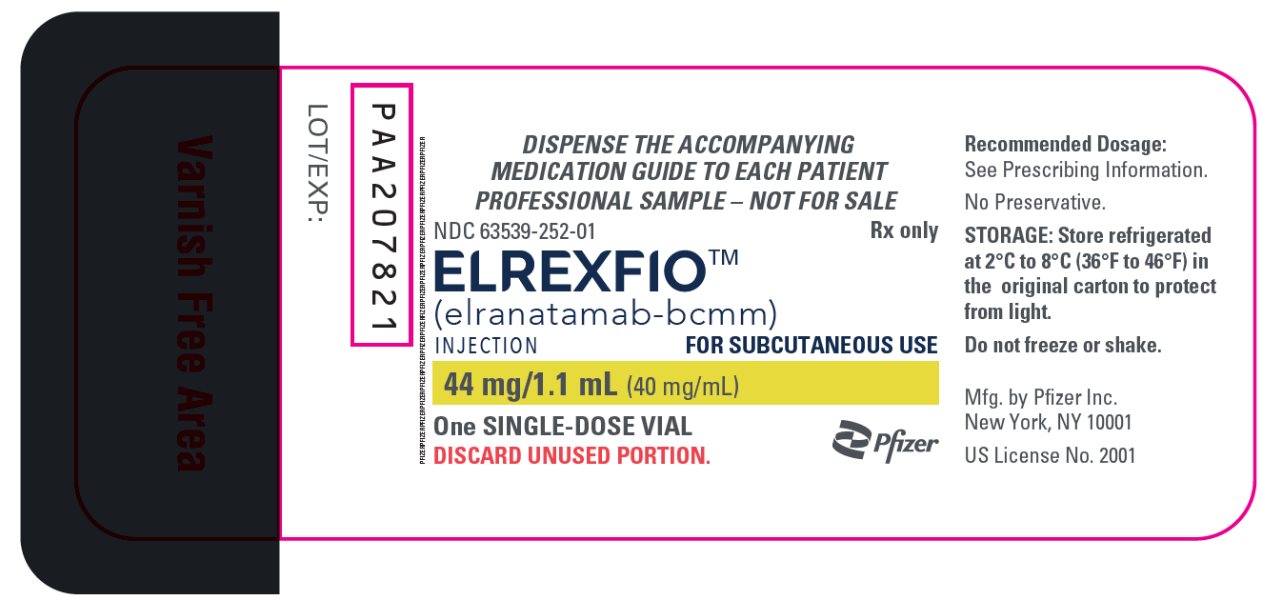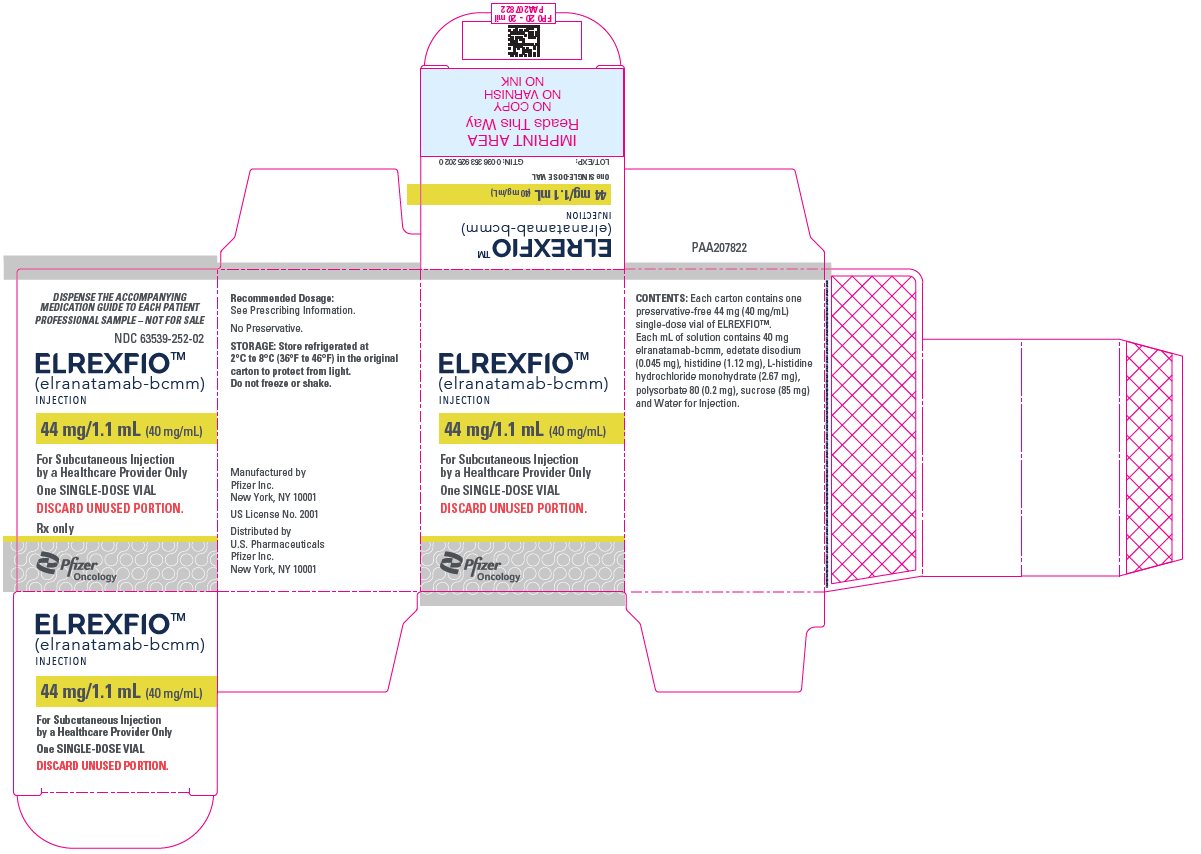 DRUG LABEL: Elrexfio
NDC: 63539-252 | Form: INJECTION, SOLUTION
Manufacturer: U.S. Pharmaceuticals
Category: prescription | Type: HUMAN PRESCRIPTION DRUG LABEL
Date: 20260226

ACTIVE INGREDIENTS: ELRANATAMAB 44 mg/1.1 mL
INACTIVE INGREDIENTS: HISTIDINE 1.23 mg/1.1 mL; HISTIDINE MONOHYDROCHLORIDE MONOHYDRATE 2.94 mg/1.1 mL; EDETATE DISODIUM 0.06 mg/1.1 mL; POLYSORBATE 80 0.2 mg/1.1 mL; SUCROSE 94 mg/1.1 mL; WATER

HIGHLIGHTS OF PRESCRIBING INFORMATION

These highlights do not include all the information needed to use ELREXFIO safely and effectively. See full prescribing information for ELREXFIO.
ELREXFIO® (elranatamab-bcmm) injection, for subcutaneous use
Initial U.S. Approval: 2023

RECENT MAJOR CHANGES

Dosage and Administration, Recommended Dosage (2.2) | 7/2025
Dosage and Administration, Restarting ELREXFIO After Dosage Delay (2.4) | 7/2025
Dosage and Administration, Preparation and Administration Instructions (2.6) | 7/2025

WARNING: CYTOKINE RELEASE SYNDROME and NEUROLOGIC TOXICITY including IMMUNE EFFECTOR CELL-ASSOCIATED NEUROTOXICITY SYNDROME

See full prescribing information for complete boxed warning.

- Cytokine Release Syndrome (CRS), including life-threatening or fatal reactions, can occur in patients receiving ELREXFIO. Initiate treatment with ELREXFIO step-up dosing schedule to reduce risk of CRS. Withhold ELREXFIO until CRS resolves or permanently discontinue based on severity. (2.2, 2.5, 5.1)
- Neurologic toxicity, including Immune Effector Cell-Associated Neurotoxicity Syndrome (ICANS), and serious and life-threatening reactions, can occur in patients receiving ELREXFIO. Monitor patients for signs and symptoms of neurologic toxicity, including ICANS, during treatment. Withhold ELREXFIO until the neurologic toxicity resolves or permanently discontinue based on severity. (2.5, 5.2)
- ELREXFIO is available only through a restricted program called the ELREXFIO Risk Evaluation and Mitigation Strategy (REMS). (5.3)

1 INDICATIONS AND USAGE

ELREXFIO is a bispecific B-cell maturation antigen (BCMA)-directed CD3 T‑cell engager indicated for the treatment of adult patients with relapsed or refractory multiple myeloma who have received at least four prior lines of therapy including a proteasome inhibitor, an immunomodulatory agent, and an anti-CD38 monoclonal antibody.

This indication is approved under accelerated approval based on response rate and durability of response. Continued approval for this indication may be contingent upon verification of clinical benefit in a confirmatory trial(s). (1)

2 DOSAGE AND ADMINISTRATION

 | ELREXFIO Dosing Schedule (2.2)
Dosing Schedule | Day | ELREXFIO Dose
Step-up Dosing Schedule | Day 1 | Step-up dose 1 | 12 mg
Step-up Dosing Schedule | Day 4 | Step-up dose 2 | 32 mg
Step-up Dosing Schedule | Day 8 | First treatment dose | 76 mg
Weekly Dosing Schedule | One week after first treatment dose and weekly thereafter through week 24 | Subsequent treatment doses | 76 mg
Biweekly (Every 2 Week) Dosing Schedule [Responders only week 25 onward.] | Week 25 and every 2 weeks thereafter through week 48 | Subsequent treatment doses | 76 mg
Every 4 Week Dosing Schedule [In patients who have maintained the response following 24 weeks of treatment at the biweekly dosing schedule.] | Week 49 and every 4 weeks thereafter | Subsequent treatment doses | 76 mg

- Patients should be hospitalized for 48 hours after administration of the first step-up dose, and for 24 hours after administration of the second step-up dose. (2.1)
- For subcutaneous injection only. (2.2)
- Administer pre-treatment medications as recommended. (2.3)
- See Full Prescribing Information for instructions on preparation and administration. (2.6)

3 DOSAGE FORMS AND STRENGTHS

Injection:

- 76 mg/1.9 mL (40 mg/mL) in a single-dose vial. (3)
- 44 mg/1.1 mL (40 mg/mL) in a single-dose vial. (3)

4 CONTRAINDICATIONS

None. (4)

5 WARNINGS AND PRECAUTIONS

- Infections: Can cause severe, life-threatening, or fatal infections. Monitor patients for signs and symptoms of infection and treat appropriately. Do not initiate treatment in patients with active infections. (5.4)
- Neutropenia: Monitor complete blood cell counts at baseline and periodically during treatment. (5.5)
- Hepatotoxicity: Can cause elevated ALT, AST, and bilirubin. Monitor liver enzymes and bilirubin at baseline and during treatment as clinically indicated. (5.6)
- Embryo-Fetal Toxicity: May cause fetal harm. Advise females of reproductive potential of the potential risk to the fetus and to use effective contraception. (5.7, 8.1. 8.3)

6 ADVERSE REACTIONS

Most common adverse reactions (incidence ≥20%) are CRS, fatigue, injection site reaction, diarrhea, upper respiratory tract infection, musculoskeletal pain, pneumonia, decreased appetite, rash, cough, nausea, and pyrexia.

The most common Grade 3 to 4 laboratory abnormalities (≥30%) are decreased lymphocytes, decreased neutrophils, decreased hemoglobin, decreased white blood cells, and decreased platelets. (6.1)

To report SUSPECTED ADVERSE REACTIONS, contact Pfizer Inc. at 1-800-438-1985 or FDA at 1-800-FDA-1088 or www.fda.gov/medwatch.

8 USE IN SPECIFIC POPULATIONS

Lactation: Advise not to breastfeed. (8.2)

FULL PRESCRIBING INFORMATION

WARNING: CYTOKINE RELEASE SYNDROME and NEUROLOGIC TOXICITY including IMMUNE EFFECTOR CELL-ASSOCIATED NEUROTOXICITY SYNDROME

- Cytokine Release Syndrome (CRS), including life-threatening or fatal reactions, can occur in patients receiving ELREXFIO. Initiate treatment with ELREXFIO step-up dosing schedule to reduce the risk of CRS. Withhold ELREXFIO until CRS resolves or permanently discontinue based on severity [see Dosage and Administration (2.2, 2.5), Warnings and Precautions (5.1)].
- Neurologic toxicity, including Immune Effector Cell-Associated Neurotoxicity Syndrome (ICANS), and serious and life-threatening reactions, can occur in patients receiving ELREXFIO. Monitor patients for signs and symptoms of neurologic toxicity, including ICANS, during treatment. Withhold ELREXFIO until the neurologic toxicity resolves or permanently discontinue based on severity [see Dosage and Administration (2.5), Warnings and Precautions (5.2)].
- Because of the risk of CRS and neurologic toxicity, including ICANS, ELREXFIO is available only through a restricted program under a Risk Evaluation and Mitigation Strategy (REMS) called ELREXFIO REMS [see Warnings and Precautions (5.3)].

1 INDICATIONS AND USAGE

ELREXFIO is indicated for the treatment of adult patients with relapsed or refractory multiple myeloma who have received at least four prior lines of therapy, including a proteasome inhibitor, an immunomodulatory agent, and an anti-CD38 monoclonal antibody.

This indication is approved under accelerated approval based on response rate and durability of response [see Clinical Studies (14)]. Continued approval for this indication may be contingent upon verification of clinical benefit in a confirmatory trial(s).

2 DOSAGE AND ADMINISTRATION

2.1 Important Dosing Information

Administer ELREXFIO subcutaneously according to the step-up dosing schedule to reduce the incidence and severity of cytokine release syndrome (CRS).

Administer pre-treatment medications prior to each dose in the ELREXFIO step-up dosing schedule, which includes step-up dose 1, step-up dose 2, and the first treatment dose as recommended [see Dosage and Administration (2.2, 2.3)].

ELREXFIO should only be administered by a qualified healthcare professional with appropriate medical support to manage severe reactions such as CRS and neurologic toxicity, including ICANS [see Warnings and Precautions (5.1, 5.2)].

Due to the risk of CRS, patients should be hospitalized for 48 hours after administration of the first step-up dose, and for 24 hours after administration of the second step-up dose.

2.2 Recommended Dosage

For subcutaneous injection only.

The recommended dosing schedule for ELREXFIO is provided in Table 1. The recommended dosages of ELREXFIO subcutaneous injection are: step-up dose 1 of 12 mg on Day 1, step-up dose 2 of 32 mg on Day 4, followed by the first treatment dose of 76 mg on Day 8, and then 76 mg weekly thereafter through week 24.

For patients who have received at least 24 weeks of treatment with ELREXFIO and have achieved a response [partial response (PR) or better] and maintained this response for at least 2 months, the dose interval should transition to an every two-week schedule. For patients who have received at least 24 weeks of treatment with ELREXFIO at the every two-week dosing schedule and have maintained the response, the dose interval should transition to an every four-week schedule.

Continue treatment with ELREXFIO until disease progression or unacceptable toxicity.

Administer pre-treatment medications prior to each dose in the ELREXFIO step-up dosing schedule, which includes step-up dose 1, step-up dose 2, and the first treatment dose as recommended [see Dosage and Administration (2.3)].

Table 1. ELREXFIO Dosing Schedule
Dosing Schedule | Day | ELREXFIO Dose
Step-up Dosing Schedule | Day 1 [Administer pre-treatment medications prior to each dose in the ELREXFIO step-up dosing schedule, which includes step-up dose 1, step-up dose 2, and the first treatment dose [see Dosage and Administration (2.3)].] | Step-up dose 1 | 12 mg
Step-up Dosing Schedule | Day 4 [A minimum of 2 days should be maintained between step-up dose 1 (12 mg) and step-up dose 2 (32 mg).] | Step-up dose 2 | 32 mg
Step-up Dosing Schedule | Day 8 [A minimum of 3 days should be maintained between step-up dose 2 (32 mg) and the first treatment (76 mg) dose.] | First treatment dose | 76 mg
Weekly Dosing Schedule | One week after first treatment dose and weekly thereafter [A minimum of 6 days should be maintained between treatment doses.] through week 24 | Subsequent treatment doses | 76 mg
Biweekly (Every 2 Week) Dosing Schedule; *Responders only week 25 onward | Week 25 and every 2 weeks thereafter; through week 48 | Subsequent treatment doses | 76 mg
Every 4 Week Dosing Schedule; *In patients who have maintained the response following 24 weeks of treatment at the biweekly dosing schedule | Week 49 and every 4 weeks thereafter | Subsequent treatment doses | 76 mg
Note: See Table 2 for recommendations on restarting ELREXFIO after dose delays.

2.3 Recommended Pre-treatment Medications

Administer the following pre-treatment medications approximately 1 hour before the first three doses of ELREXFIO in the step-up dosing schedule, which includes step-up dose 1, step-up dose 2, and the first treatment dose as described in Table 1 to reduce the risk of CRS [see Warnings and Precautions (5.1)]:

- acetaminophen (or equivalent) 650 mg orally
- dexamethasone (or equivalent) 20 mg orally or intravenously
- diphenhydramine (or equivalent) 25 mg orally

2.4 Restarting ELREXFIO After Dosage Delay

If a dose of ELREXFIO is delayed, restart therapy based on the recommendations listed in Table 2 and resume the dosing schedule accordingly [see Dosage and Administration (2.2)]. Administer pre-treatment medications as indicated in Table 2.

Table 2. Recommendation for Restarting Therapy with ELREXFIO After Dosage Delay
Last Dose Administered | Time Since the Last Dose Administered | Action for Next Dose
Step-up dose 1 (12 mg) | 2 weeks or less (≤14 days) | Restart ELREXFIO at step-up dose 2 (32 mg). [Administer pre-treatment medications prior to the ELREXFIO dose [see Dosage and Administration (2.3)].] If tolerated, increase to 76 mg 4 days later.
Step-up dose 1 (12 mg) | Greater than 2 weeks (>14 days) | Restart ELREXFIO step-up dosing schedule at step-up dose 1 (12 mg).
Step-up dose 2 (32 mg) | 2 weeks or less (≤14 days) | Restart ELREXFIO at 76 mg.
Step-up dose 2 (32 mg) | Greater than 2 weeks to less than or equal to 4 weeks (15 days to ≤28 days) | Restart ELREXFIO at step-up dose 2 (32 mg). If tolerated, increase to 76 mg 1 week later.
Step-up dose 2 (32 mg) | Greater than 4 weeks (>28 days) | Restart ELREXFIO step-up dosing schedule at step-up dose 1 (12 mg).
Any weekly treatment dose (76 mg) | 8 weeks or less (≤56 days) | Restart ELREXFIO at 76 mg.
Any weekly treatment dose (76 mg) | Greater than 8 weeks to less or equal to 12 weeks (57 days to ≤84 days) [Consider benefit-risk of restarting ELREXFIO in patients who require a dose delay of more than 56 days due to an adverse reaction.] | Restart ELREXFIO at step-up dose 2 (32 mg). If tolerated, increase to 76 mg 1 week later.
Any weekly treatment dose (76 mg) | Greater than 12 weeks (>84 days) | Restart ELREXFIO step-up dosing schedule at step-up dose 1 (12 mg).
Any biweekly or every-4-week treatment dose (76 mg) | 12 weeks or less (≤84 days) | Restart ELREXFIO at 76 mg.
 | Greater than 12 weeks (>84 days) | Restart ELREXFIO step-up dosing schedule at step-up dose 1 (12 mg).

2.5 Dosage Modifications for Adverse Reactions

Dosage reductions of ELREXFIO are not recommended.

Dosage delays may be required to manage toxicities related to ELREXFIO [see Warnings and Precautions (5)]. Recommendations on restarting ELREXFIO after a dose delay are provided in Table 2.

See Table 3 and Table 4 for recommended actions for adverse reactions of CRS and ICANS, respectively. See Table 5 for recommended actions for neurologic toxicity excluding ICANS and Table 6 for recommended actions for other adverse reactions following administration of ELREXFIO. Consider further management per current practice guidelines.

Management of CRS, Neurologic Toxicity Including ICANS

Cytokine Release Syndrome (CRS)

Management recommendations for CRS are summarized in Table 3.

Identify CRS based on clinical presentation [see Warnings and Precautions (5.1)]. Evaluate and treat other causes of fever, hypoxia, and hypotension.

If CRS is suspected, withhold ELREXFIO until CRS resolves. Manage CRS according to the recommendations in Table 3 and consider further management per current practice guidelines. Administer supportive therapy for CRS, which may include intensive care for severe or life-threatening CRS. Consider laboratory testing to monitor for disseminated intravascular coagulation (DIC), hematology parameters, as well as pulmonary, cardiac, renal, and hepatic function.

Table 3. Recommendations for Management of CRS
Grade [Based on American Society for Transplantation and Cellular Therapy (ASTCT) 2019 grading criteria for CRS.] | Presenting Symptoms | Actions
Grade 1 | Temperature ≥100.4 °F (38 °C) [Attributed to CRS. Fever may not always be present concurrently with hypotension or hypoxia as it may be masked by interventions such as antipyretics or anti-cytokine therapy.] | - Withhold ELREXFIO until CRS resolves. [See Table 2 for recommendations on restarting ELREXFIO after dose delays.] - Administer pretreatment medications prior to next dose of ELREXFIO.
Grade 2 | Temperature ≥100.4 °F (38 °C) with either:; - Hypotension responsive to fluid and not requiring vasopressors, and/or - Oxygen requirement of low-flow nasal cannula [Low-flow nasal cannula is ≤6 L/min, and high-flow nasal cannula is >6 L/min.] or blow-by | - Withhold ELREXFIO until CRS resolves. - Monitor patients daily for 48 hours following the next dose of ELREXFIO. Instruct patients to remain within proximity of a healthcare facility, and consider hospitalization. - Administer pretreatment medications prior to next dose of ELREXFIO.
Grade 3; (First occurrence) | Temperature ≥100.4 °F (38 °C) with either:; - Hypotension requiring one vasopressor with or without vasopressin, and/or - Oxygen requirement of high-flow nasal cannula, facemask, non-rebreather mask, or Venturi mask | - Withhold ELREXFIO until CRS resolves. - Provide supportive therapy, which may include intensive care. - Patients should be hospitalized for 48 hours following the next dose of ELREXFIO. - Administer pretreatment medications prior to next dose of ELREXFIO.
Grade 3 (Recurrent) | Temperature ≥100.4 °F (38 °C) with either:; - Hypotension requiring one vasopressor with or without vasopressin, and/or - Oxygen requirement of high-flow nasal cannula, facemask, non-rebreather mask, or Venturi mask | - Permanently discontinue therapy with ELREXFIO. - Provide supportive therapy, which may include intensive care.
Grade 4 | Temperature ≥100.4 °F (38 °C) with either:; - Hypotension requiring multiple vasopressors (excluding vasopressin), and/or - Oxygen requirement of positive pressure (e.g., continuous positive airway pressure [CPAP], bilevel positive airway pressure [BiPAP], intubation, and mechanical ventilation) | - Permanently discontinue therapy with ELREXFIO. - Provide supportive therapy, which may include intensive care.

Neurologic Toxicity Including ICANS

Management recommendations for ICANS and neurologic toxicity are summarized in Table 4 and Table 5.

At the first sign of neurologic toxicity, including ICANS, withhold ELREXFIO and consider neurology evaluation. Rule out other causes of neurologic symptoms. Provide supportive therapy, which may include intensive care, for severe or life-threatening neurologic toxicities, including ICANS [see Warnings and Precautions (5.2)]. Manage ICANS according to the recommendations in Table 4 and consider further management per current practice guidelines.

Table 4. Recommendations for Management of ICANS
Grade [Based on American Society for Transplantation and Cellular Therapy (ASTCT) 2019 grading criteria for ICANS.] | Presenting Symptoms [Management is determined by the most severe event, not attributable to any other cause.] | Actions
Grade 1 | ICE score 7-9 [If patient is arousable and able to perform Immune Effector Cell-Associated Encephalopathy (ICE) Assessment, assess: Orientation (oriented to year, month, city, hospital = 4 points); Naming (name 3 objects, e.g., point to clock, pen, button = 3 points); Following Commands (e.g., “show me 2 fingers” or “close your eyes and stick out your tongue” = 1 point); Writing (ability to write a standard sentence = 1 point); and Attention (count backwards from 100 by ten = 1 point). If patient is unarousable and unable to perform ICE Assessment (Grade 4 ICANS) = 0 points.] Or depressed level of consciousness [Not attributable to any other cause.] : awakens spontaneously. | - Withhold ELREXFIO until ICANS resolves. [See Table 2 for recommendations on restarting ELREXFIO after dose delays.] - Monitor neurologic symptoms and consider consultation with a neurologist and other specialists for further evaluation and management. - Consider non-sedating, anti-seizure medications (e.g., levetiracetam) for seizure prophylaxis.
Grade 2 | ICE score 3-6 Or depressed level of consciousness: awakens to voice. | - Withhold ELREXFIO until ICANS resolves. - Administer dexamethasone [All references to dexamethasone administration are dexamethasone or equivalent medications.] 10 mg intravenously every 6 hours. Continue dexamethasone use until resolution to Grade 1 or less, then taper. - Monitor neurologic symptoms and consider consultation with a neurologist and other specialists for further evaluation and management. - Consider non-sedating, anti-seizure medications (e.g., levetiracetam) for seizure prophylaxis. - Monitor patients daily for 48 hours following the next dose of ELREXFIO. Instruct patients to remain within proximity of a healthcare facility, and consider hospitalization.
Grade 3; (First occurrence) | ICE score 0-2 or depressed level of consciousness: awakens only to tactile stimulus, or seizures, either:; - any clinical seizure, focal or generalized, that resolves rapidly, or - non-convulsive seizures on electroencephalogram (EEG) that resolve with intervention,; or raised intracranial pressure: focal/local edema on neuroimaging | - Withhold ELREXFIO until ICANS resolves. - Administer dexamethasone 10 mg intravenously every 6 hours. Continue dexamethasone use until resolution to Grade 1 or less, then taper. - Monitor neurologic symptoms and consider consultation with a neurologist and other specialists for further evaluation and management. - Consider non-sedating, anti-seizure medications (e.g., levetiracetam) for seizure prophylaxis. - Provide supportive therapy, which may include intensive care. - Patients should be hospitalized for 48 hours following the next dose of ELREXFIO.
Grade 3 (recurrent) | ICE score 0-2 or depressed level of consciousness: awakens only to tactile stimulus, or seizures, either:; - any clinical seizure, focal or generalized, that resolves rapidly, or - non-convulsive seizures on electroencephalogram (EEG) that resolve with intervention,; or raised intracranial pressure: focal/local edema on neuroimaging | - Permanently discontinue ELREXFIO. - Administer dexamethasone 10 mg intravenously every 6 hours. Continue dexamethasone use until resolution to Grade 1 or less, then taper. - Monitor neurologic symptoms and consider consultation with a neurologist and other specialists for further evaluation and management. - Consider non-sedating, anti-seizure medications (e.g., levetiracetam) for seizure prophylaxis. - Provide supportive therapy, which may include intensive care.
Grade 4 | ICE score 0 Or, depressed level of consciousness either:; - patient is unarousable or requires vigorous or repetitive tactile stimuli to arouse, or - stupor or coma,; or seizures, either:; - life-threatening prolonged seizure (>5 minutes), or - repetitive clinical or electrical seizures without return to baseline in between,; or motor findings:; - deep focal motor weakness such as hemiparesis or paraparesis,; or raised intracranial pressure/cerebral edema, with signs/symptoms such as:; - diffuse cerebral edema on neuroimaging, or - decerebrate or decorticate posturing, or - cranial nerve VI palsy, or - papilledema, or - Cushing’s triad | - Permanently discontinue ELREXFIO. - Administer dexamethasone 10 mg intravenously every 6 hours. Continue dexamethasone use until resolution to Grade 1 or less, then taper. - Alternatively, consider administration of methylprednisolone 1,000 mg per day intravenously for 3 days. - Monitor neurologic symptoms and consider consultation with a neurologist and other specialists for further evaluation and management. - Consider non-sedating, anti-seizure medications (e.g., levetiracetam) for seizure prophylaxis. - Provide supportive therapy, which may include intensive care.

Table 5. Recommendations for Management of Neurologic Toxicity, Excluding ICANS
Adverse Reaction | Severity | Actions
Neurologic Toxicity (excluding ICANS) | Grade 1 | - Withhold ELREXFIO until neurologic toxicity symptoms resolve or stabilize.
Neurologic Toxicity (excluding ICANS) | Grade 2; Grade 3 (First occurrence) | - Withhold ELREXFIO until neurologic toxicity symptoms improve to Grade 1 or less. - Provide supportive therapy.
Neurologic Toxicity (excluding ICANS) | Grade 3 (Recurrent); Grade 4 | - Permanently discontinue ELREXFIO. - Provide supportive therapy, which may include intensive care.

Table 6. Recommended Dosage Modifications for Other Adverse Reactions
Adverse Reactions | Severity | Actions
Hematologic Adverse Reactions; [see Warnings and Precautions (5.5)] | Absolute neutrophil count less than 0.5 x 10^9/L | - Withhold ELREXFIO until absolute neutrophil count is 0.5 x 10^9/L or higher. [See Table 2 for recommendations on restarting ELREXFIO after dose delays.]
Hematologic Adverse Reactions; [see Warnings and Precautions (5.5)] | Febrile neutropenia | - Withhold ELREXFIO until absolute neutrophil count is 1 x 10^9/L or higher and fever resolves.
Hematologic Adverse Reactions; [see Warnings and Precautions (5.5)] | Hemoglobin less than 8 g/dL | - Withhold ELREXFIO until hemoglobin is 8 g/dL or higher.
Hematologic Adverse Reactions; [see Warnings and Precautions (5.5)] | Platelet count less than 25,000/mcL; Platelet count between 25,000/mcL and 50,000/mcL with bleeding | - Withhold ELREXFIO until platelet count is 25,000/mcL or higher and no evidence of bleeding.
Infections and Other Non-hematologic Adverse Reactions [Based on National Cancer Institute Common Terminology Criteria for Adverse Events (NCI-CTCAE), Version 5.0.]; [see Warnings and Precautions (5.4, 5.6) and Adverse Reactions (6.1)] | Grade 3 | - Withhold ELREXFIO until adverse reaction improves to ≤Grade 1 or baseline.
Infections and Other Non-hematologic Adverse Reactions [Based on National Cancer Institute Common Terminology Criteria for Adverse Events (NCI-CTCAE), Version 5.0.]; [see Warnings and Precautions (5.4, 5.6) and Adverse Reactions (6.1)] | Grade 4 | - Consider permanent discontinuation of ELREXFIO. - If ELREXFIO is not permanently discontinued, withhold subsequent treatment doses of ELREXFIO (e.g., doses administered after ELREXFIO step-up dosing schedule) until adverse reaction improves to Grade 1 or less.

2.6 Preparation and Administration Instructions

ELREXFIO is intended for subcutaneous use by a healthcare provider only.

ELREXFIO should be administered by a healthcare provider with adequate medical personnel and appropriate medical equipment to manage severe reactions, including CRS and neurologic toxicity, including ICANS [see Warnings and Precautions (5.1, 5.2)].

ELREXFIO 76 mg/1.9 mL (40 mg/mL) vial and 44 mg/1.1 mL (40 mg/mL) vial are supplied as ready-to-use solution that do not need dilution prior to administration.

ELREXFIO is a clear to slightly opalescent, and colorless to pale brown liquid solution. Parenteral drug products should be inspected visually for particulate matter and discoloration prior to administration, whenever solution and container permit. Do not administer if solution is discolored or contains particulate matter.

Use aseptic technique to prepare and administer ELREXFIO.

Preparation

ELREXFIO vials are for one-time use in a single patient and do not contain any preservatives.

Prepare ELREXFIO following the instructions below (see Table 7) depending on the required dose.

Table 7. Injection Volumes
Total Dose (mg) | Volume of Injection
12 mg | 0.3 mL
32 mg | 0.8 mL
76 mg | 1.9 mL

Remove the appropriate strength ELREXFIO vial from refrigerated storage [2 °C to 8 °C (36 °F to 46 °F)]. Once removed from refrigerated storage, equilibrate ELREXFIO to ambient temperature [15 °C to 30 °C (59 °F to 86 °F)]. Do not warm ELREXFIO in any other way.

Withdraw the required injection volume of ELREXFIO from the vial into an appropriately sized syringe with stainless steel injection needles (30G or wider) and polypropylene or polycarbonate syringe material. Discard unused portion.

Administration

Inject the required volume of ELREXFIO into the subcutaneous tissue of the abdomen (preferred injection site). Alternatively, ELREXFIO may be injected into the subcutaneous tissue at other sites (e.g., thigh).

Do not inject into tattoos or scars or areas where the skin is red, bruised, tender, hard or not intact.

Storage of Prepared Syringe

If the prepared dosing syringe is not used immediately, the syringe may be stored refrigerated between 2 °C to 8 °C (36 °F to 46 °F) for a maximum of 72 hours or between 8 °C to 25 °C (46 °F to 77 °F) for a maximum of 24 hours. Once removed from refrigerated storage, the prepared syringe must be used or discarded.

3 DOSAGE FORMS AND STRENGTHS

ELREXFIO injection is a clear to slightly opalescent, and colorless to pale brown liquid solution available as:

- 76 mg/1.9 mL (40 mg/mL) in a single-dose vial
- 44 mg/1.1 mL (40 mg/mL) in a single-dose vial

4 CONTRAINDICATIONS

None.

5 WARNINGS AND PRECAUTIONS

5.1 Cytokine Release Syndrome (CRS)

ELREXFIO can cause CRS, including life-threatening or fatal reactions [see Adverse Reactions (6.1)].

In the clinical trial, CRS occurred in 58% of patients who received ELREXFIO at the recommended dosing schedule [see Dosage and Administration (2.2)], with Grade 1 CRS in 44% of patients, Grade 2 CRS in 14% of patients, and Grade 3 CRS in 0.5% of patients. Recurrent CRS occurred in 13% of patients. Most patients experienced CRS after the first step-up dose (43%) or the second step-up dose (19%), with 7% of patients having CRS after the first treatment dose and 1.6% of patients after a subsequent dose. The median time to onset of CRS was 2 (range: 1 to 9) days after the most recent dose, with a median duration of 2 (range: 1 to 19) days.

Clinical signs and symptoms of CRS may include, but are not limited to, fever, hypoxia, chills, hypotension, tachycardia, headache, and elevated liver enzymes.

Initiate therapy according to the ELREXFIO step-up dosing schedule to reduce risk of CRS and monitor patients following administration of ELREXFIO accordingly [see Dosage and Administration (2.2, 2.5)]. Administer pre-treatment medications prior to each dose in the step-up dosing schedule to reduce risk of CRS [see Dosage and Administration (2.3)].

Counsel patients to seek medical attention should signs or symptoms of CRS occur. At the first sign of CRS, evaluate patients immediately for hospitalization. Manage CRS according to the recommendations and consider further management per current practice guidelines. Withhold or permanently discontinue ELREXFIO based on severity [see Dosage and Administration (2.5)].

ELREXFIO is available only through a restricted program under a REMS [see Warnings and Precautions (5.3)].

5.2 Neurologic Toxicity, Including Immune Effector Cell-Associated Neurotoxicity Syndrome (ICANS)

ELREXFIO can cause serious or life-threatening neurologic toxicity, including ICANS [see Adverse Reactions (6.1)].

In the clinical trial, neurologic toxicity occurred in 59% of patients who received ELREXFIO at the recommended dosing schedule [see Dosage and Administration (2.2)], with Grade 3 or 4 neurologic toxicity occurring in 7% of patients. Neurologic toxicities included headache (18%), encephalopathy (15%), motor dysfunction (13%), sensory neuropathy (13%), and Guillain-Barré Syndrome (0.5%).

In the clinical trial, ICANS occurred in 3.3% of patients who received ELREXFIO at the recommended dosing schedule [see Dosage and Administration (2.2)]. Most patients had ICANS after the first step-up dose (2.7%), 1 (0.5%) patient had ICANS after the second step-up dose and 1 (0.5%) patient had ICANS after subsequent dose(s). Recurrent ICANS occurred in 1.1% of patients. The median time to onset was 3 (range: 1 to 4) days after the most recent dose, with a median duration of 2 (range: 1 to 18) days. The most frequent clinical manifestations of ICANS included a depressed level of consciousness and Grade 1 or Grade 2 Immune Effector Cell-Associated Encephalopathy (ICE) scores. The onset of ICANS can be concurrent with CRS, following resolution of CRS, or in the absence of CRS.

Counsel patients to seek medical attention should signs or symptoms of neurologic toxicity occur. Monitor patients for signs and symptoms of neurologic toxicities during treatment with ELREXFIO. At the first sign of neurologic toxicity, including ICANS, evaluate and treat patients immediately based on severity. Withhold or permanently discontinue ELREXFIO based on severity per recommendations [see Dosage and Administration (2.5)] and consider further management per current practice guidelines.

Due to the potential for neurologic toxicity including ICANS, patients receiving ELREXFIO are at risk of depressed level of consciousness. Advise patients not to drive or operate heavy or potentially dangerous machinery for 48 hours after completing each of the 2 step-up doses and the first treatment dose within the ELREXFIO step-up dosing schedule and in the event of new onset of any neurological toxicity symptoms until symptoms resolve [see Dosage and Administration (2.2)].

ELREXFIO is available only through a restricted program under a REMS [see Warnings and Precautions (5.3)].

5.3 ELREXFIO REMS

ELREXFIO is available only through a restricted program under a REMS called the ELREXFIO REMS because of the risks of CRS and neurologic toxicity, including ICANS [see Warnings and Precautions (5.1, 5.2)].

Notable requirements of the ELREXFIO REMS include the following:

- Prescribers must be certified with the program by enrolling and completing training.
- Prescribers must counsel patients receiving ELREXFIO about the risk of CRS and neurologic toxicity, including ICANS, and provide patients with ELREXFIO Patient Wallet Card.
- Pharmacies and healthcare settings that dispense ELREXFIO must be certified with the ELREXFIO REMS program and must verify prescribers are certified through the ELREXFIO REMS program.
- Wholesalers and distributers must only distribute ELREXFIO to certified pharmacies or healthcare settings.

Further information about the ELREXFIO REMS program is available at www.ELREXFIOREMS.com or by telephone at 1‑844‑923‑7845.

5.4 Infections

ELREXFIO can cause severe, life-threatening, or fatal infections. In the clinical trial, in patients who received ELREXFIO according to the recommended dosing schedule, serious infections, including opportunistic infections, occurred in 42% of patients, with Grade 3 or 4 infections in 31%, and fatal infections in 7%. The most common serious infections reported (≥5%) were pneumonia and sepsis [see Adverse Reactions (6.1)].

Do not initiate treatment with ELREXFIO in patients with active infections. Monitor patients for signs and symptoms of infection prior to and during treatment with ELREXFIO and treat appropriately. Withhold or permanently discontinue ELREXFIO based on severity [see Dosage and Administration (2.5)]. Administer prophylactic antimicrobial and anti-viral medications according to current practice guidelines. Consider treatment with subcutaneous or intravenous immunoglobulin (IVIG) as appropriate.

5.5 Neutropenia

ELREXFIO can cause neutropenia and febrile neutropenia. In patients who received ELREXFIO at the recommended dose in the clinical trial, decreased neutrophils occurred in 62% of patients, with Grade 3 or 4 decreased neutrophils in 51%. Febrile neutropenia occurred in 2.2% of patients [see Adverse Reactions (6.1)].

Monitor complete blood cell counts at baseline and periodically during treatment. Provide supportive care according to current practice guidelines. Monitor patients with neutropenia for signs of infection. Withhold ELREXFIO based on severity [see Dosage and Administration (2.5)].

5.6 Hepatotoxicity

ELREXFIO can cause hepatotoxicity. In the clinical trial, elevated ALT occurred in 36% of patients, with Grade 3 or 4 ALT elevation occurring in 3.8%; elevated AST occurred in 40% of patients, with Grade 3 or 4 AST elevation occurring in 6%. Grade 3 or 4 total bilirubin elevations occurred in 0.5% of patients [see Adverse Reactions (6.1)]. Liver enzyme elevation can occur with or without concurrent CRS.

Monitor liver enzymes and bilirubin at baseline and during treatment as clinically indicated. Withhold ELREXFIO or consider permanent discontinuation of ELREXFIO based on severity [see Dosage and Administration (2.5)].

5.7 Embryo-Fetal Toxicity

Based on its mechanism of action, ELREXFIO may cause fetal harm when administered to a pregnant woman. Advise pregnant women of the potential risk to the fetus. Advise females of reproductive potential to use effective contraception during treatment with ELREXFIO and for 4 months after the last dose [see Use in Specific Populations (8.1, 8.3)].

6 ADVERSE REACTIONS

The following adverse reactions are discussed elsewhere in labeling:

- Cytokine Release Syndrome [see Warnings and Precautions (5.1)].
- Neurologic Toxicity, Including ICANS [see Warnings and Precautions (5.2)].
- Infections [see Warnings and Precautions (5.4)].
- Neutropenia [see Warnings and Precautions (5.5)].
- Hepatotoxicity [see Warnings and Precautions (5.6)].

6.1 Clinical Trials Experience

Because clinical trials are conducted under widely varying conditions, adverse reaction rates observed in the clinical trials of a drug cannot be directly compared to rates in the clinical trials of another drug and may not reflect the rates observed in practice.

Relapsed/Refractory Multiple Myeloma

MagnetisMM-3

The safety of ELREXFIO was evaluated in MagnetisMM-3 [see Clinical Studies (14)]. The safety population described (n = 183) includes patients who received the recommended dosage regimen of 12 mg subcutaneously on Day 1, 32 mg on Day 4, and 76 mg once weekly starting on Day 8. Among patients who received ELREXFIO, 42% were exposed for 6 months or longer and 9% were exposed for one year or longer.

The median age of patients who received ELREXFIO was 68 years (range: 36 to 88 years); 48% were female; 61% were White, 10% were Hispanic/Latino, 9% were Asian, and 6% were Black or African American.

Serious adverse reactions occurred in 68% of patients who received ELREXFIO at the recommended dosing schedule. Serious adverse reactions in >2% of patients included pneumonia (25%), sepsis (13%), CRS (13%), upper respiratory tract infection (4.4%), acute kidney injury (3.8%), urinary tract infection (3.3%), COVID-19 (3.3%), encephalopathy (3.3%), pyrexia (2.2%), and febrile neutropenia (2.2%). Fatal adverse reactions occurred in 10% of patients including pneumonia (3.3%), sepsis (2.7%), acute respiratory distress syndrome (0.5%), cardio-respiratory arrest (0.5%), cardiogenic shock (0.5%), cardiopulmonary failure (0.5%), COVID-19 (0.5%), failure to thrive (0.5%), and pulmonary embolism (0.5%).

Permanent discontinuations of ELREXFIO due to an adverse reaction occurred in 17% of patients. Adverse reactions which resulted in permanent discontinuation of ELREXFIO in >2% of patients included septic shock (2.2%).

Dosage interruptions of ELREXFIO due to an adverse reaction occurred in 73% of patients. Adverse reactions which resulted in dose interruptions of ELREXFIO in >5% of patients included neutropenia, pneumonia, COVID-19, upper respiratory tract infection, thrombocytopenia, and anemia.

The most common adverse reactions (≥20%) were CRS, fatigue, injection site reaction, diarrhea, upper respiratory tract infection, musculoskeletal pain, pneumonia, decreased appetite, rash, cough, nausea, and pyrexia. The most common Grade 3 to 4 laboratory abnormalities (≥30%) were decreased lymphocytes, decreased neutrophils, decreased hemoglobin, decreased white blood cells, and decreased platelets.

Table 8 summarizes adverse reactions in MagnetisMM-3.

Table 8. Adverse Reactions (≥10%) in Patients with Relapsed or Refractory Multiple Myeloma Who Received ELREXFIO in MagnetisMM-3
System Organ Class; Preferred Term | ELREXFIO; N = 183
 | All Grades; (%) | Grade 3 or 4; (%)
Immune system disorders
Cytokine release syndrome | 58 | 0.5 [Only grade 3 adverse reactions occurred.]
Hypogammaglobulinemia [Includes other related terms.] | 13 | 2.2
General disorders and site administration conditions
Fatigue | 43 | 6
Injection site reaction | 37 | 0
Pyrexia | 21 | 2.7
Edema | 18 | 1.1
Gastrointestinal disorders
Diarrhea | 36 | 1.1
Nausea | 21 | 0
Constipation | 14 | 0
Vomiting | 14 | 0
Infections
Upper respiratory tract infection | 36 | 4.9
Pneumonia [Pneumonia includes COVID-19 pneumonia, lower respiratory tract infection, lower respiratory tract infection viral, pneumocystis jirovecii pneumonia, pneumonia, pneumonia adenoviral, pneumonia bacterial, pneumonia cytomegaloviral, pneumonia fungal, pneumonia influenzal, pneumonia pseudomonal, pneumonia viral.] | 32 | 19
Sepsis [Sepsis includes bacteremia, device related bacteremia, device related sepsis, escherichia bacteremia, escherichia sepsis, klebsiella sepsis, pseudomonal sepsis, sepsis, septic shock, staphylococcal bacteremia, staphylococcal sepsis, streptococcal sepsis, urosepsis.] | 15 | 11
Urinary tract infection | 12 | 4.4
Musculoskeletal and connective tissue disorders
Musculoskeletal pain | 34 | 2.7
Metabolism and nutrition disorders
Decreased appetite | 26 | 1.1
Skin and Subcutaneous Tissue disorders
Rash [Rash incudes erythema, palmar-plantar erythrodysesthesia syndrome, rash, rash erythematous, rash macular, rash maculo-papular, rash pustular, symmetrical drug-related intertriginous and flexural exanthema.] | 26 | 0
Dry skin | 14 | 0
Skin exfoliation | 10 | 0
Respiratory, thoracic and mediastinal disorders
Cough | 24 | 0
Dyspnea | 15 | 3.3
Nervous system disorders
Headache | 18 | 0
Encephalopathy [Encephalopathy includes agitation, altered state of consciousness, cognitive disorder, confusional state, delirium, depressed level of consciousness, disorientation, hallucination, lethargy, memory impairment, metabolic encephalopathy, somnolence, toxic encephalopathy.] | 14 | 2.2
Sensory neuropathy [Sensory neuropathy includes burning sensation, dysesthesia, hypoesthesia, neuropathy peripheral, paresthesia, parosmia, peripheral sensorimotor neuropathy, peripheral sensory neuropathy, polyneuropathy, sensory loss.] | 13 | 0.5
Motor dysfunction [Motor dysfunction includes ataxia, balance disorder, gait disturbance, motor dysfunction, muscle contracture, muscle spasms, muscular weakness, peripheral motor neuropathy, peroneal nerve palsy, tremor.] | 14 | 1.1
Cardiac disorders
Cardiac arrhythmia | 16 | 1.6
Vascular disorders
Hemorrhage | 13 | 1.6
Psychiatric disorders
Insomnia | 13 | 0
Injury, poisoning and procedural complications
Fall | 10 | 0.5
Adverse reactions were graded based on CTCAE Version 5.0, with the exception of CRS, which was graded based on the ASTCT 2019 criteria.

Clinically relevant adverse reactions in <10% of patients who received ELREXFIO included ICANS, febrile neutropenia, Guillain-Barré syndrome, abdominal pain, acute kidney injury, COVID-19, cardiac failure, congestion, thrombosis, cytomegalovirus infection, and progressive multifocal leukoencephalopathy.

Table 9 summarizes laboratory abnormalities in MagnetisMM-3.

Table 9. Select Laboratory Abnormalities (≥30%) That Worsened from Baseline in Patients with Relapsed or Refractory Multiple Myeloma Who Received ELREXFIO in MagnetisMM-3 [Laboratory tests were graded according to NCI-CTCAE Version 5.0.]
Laboratory Abnormality | ELREXFIO [The denominator used to calculate the rate varied from 181 to 183 based on the number of patients with a baseline value and at least one post-treatment value.]
Laboratory Abnormality | All Grades (%) | Grade 3 or 4 (%)
Hematology
Lymphocyte count decreased | 91 | 84
White blood cell decreased | 69 | 40
Hemoglobin decreased | 68 | 43
Neutrophil count decreased | 62 | 51
Platelet count decreased | 61 | 32
Chemistry
Albumin decreased | 55 | 6
AST increase | 40 | 6
Creatinine increased | 38 | 3.3
Potassium decreased | 36 | 8
ALT increase | 36 | 3.8
Alkaline phosphatase increased | 34 | 1.1
Creatinine clearance decreased | 32 | 10

7 DRUG INTERACTIONS

For certain CYP substrates, minimal changes in the concentration may lead to serious adverse reactions. Monitor for toxicity or drug concentrations of such CYP substrates when co-administered with ELREXFIO.

ELREXFIO causes release of cytokines [see Clinical Pharmacology (12.2)] that may suppress activity of cytochrome P450 (CYP) enzymes, resulting in increased exposure of CYP substrates. Increased exposure of CYP substrates is more likely to occur after the first dose of ELREXFIO Day 1 and up to 14 days after the 32 mg dose on Day 4 and during and after CRS [see Warnings and Precautions (5.1)].

8 USE IN SPECIFIC POPULATIONS

8.1 Pregnancy

Risk Summary

Based on the mechanism of action, ELREXFIO may cause fetal harm when administered to a pregnant woman [see Clinical Pharmacology (12.1)]. There are no available data on the use of ELREXFIO in pregnant women to evaluate for a drug associated risk. No animal reproductive or developmental toxicity studies have been conducted with ELREXFIO. Elranatamab-bcmm causes T-cell activation and cytokine release; immune activation may compromise pregnancy maintenance. In addition, based on the finding of B-cell depletion in non-pregnant animals, elranatamab-bcmm can cause B-cell lymphocytopenia in infants exposed to elranatamab-bcmm in-utero. Human immunoglobulin (IgG) is known to cross the placenta after the first trimester of pregnancy; therefore, elranatamab-bcmm has the potential to be transmitted from the mother to the developing fetus. Advise women of the potential risk to the fetus.

ELREXFIO is associated with hypogammaglobulinemia, therefore, assessment of immunoglobulin levels in newborns of mothers treated with ELREXFIO should be considered.

In the U.S. general population, the estimated background risk of major birth defects and miscarriage in clinically recognized pregnancies is 2% to 4% and 15% to 20%, respectively.

8.2 Lactation

Risk Summary

There are no data on the presence of elranatamab-bcmm in human milk, the effects on the breastfed child, or the effects on milk production. Maternal IgG is known to be present in human milk.

Because of the potential for serious adverse reactions in a breastfed child, advise women not to breastfeed during treatment with ELREXFIO and for 4 months after the last dose.

8.3 Females and Males of Reproductive Potential

ELREXFIO may cause fetal harm when administered to a pregnant woman [see Use in Specific Populations (8.1)].

Pregnancy Testing

Verify the pregnancy status of females of reproductive potential prior to initiating treatment with ELREXFIO.

Contraception

Females

Advise females of reproductive potential to use effective contraception during treatment and for 4 months after the last dose of ELREXFIO.

8.4 Pediatric Use

The safety and effectiveness of ELREXFIO in pediatric patients have not been established.

8.5 Geriatric Use

Of the 183 patients with relapsed or refractory multiple myeloma treated with ELREXFIO in MagnetisMM-3 at the recommended dosage, 62% were 65 years of age or older, and 19% were 75 years of age or older. No overall differences in safety or effectiveness were observed in patients 65-74 years of age compared to younger patients. Clinical studies did not include sufficient numbers of patients 75 years of age or older to determine whether they respond differently from younger patients.

11 DESCRIPTION

Elranatamab-bcmm is a bispecific B-cell maturation antigen (BCMA)-directed CD3 T-cell engager. It is a bispecific, humanized immunoglobulin 2-alanine (IgG2Δa) kappa antibody derived from two monoclonal antibodies (mAbs), an anti-BCMA mAb and an anti-CD3 mAb. Each of these mAbs contributes one distinct heavy (H) chain and one distinct light (L) chain to the bispecific elranatamab-bcmm. The resulting 4-chain bispecific antibody is covalently linked via five inter-chain disulfide bonds. Elranatamab-bcmm is produced using two recombinant Chinese hamster ovary (CHO) cell lines, one that contains the DNA encoding the sequence for anti-BCMA monoclonal antibody (mAb) and one that contains the sequence for anti-CD3 mAb, which are grown separately in suspension culture using chemically-defined (CD), animal-derived component-free (ACF) media. The molecular weight of elranatamab-bcmm is approximately 148.5 kDa.

ELREXFIO® (elranatamab-bcmm) injection is a sterile, preservative-free, clear to slightly opalescent, and colorless to pale brown liquid solution for subcutaneous administration. ELREXFIO (elranatamab-bcmm) is supplied at a concentration of 40 mg/mL in either 76 mg/1.9 mL or 44 mg/1.1 mL single-dose vials. Each mL of solution contains 40 mg elranatamab-bcmm, edetate disodium (0.045 mg), histidine (1.12 mg), L-histidine hydrochloride monohydrate (2.67 mg), polysorbate 80 (0.2 mg), sucrose (85 mg) and Water for Injection. The pH is 5.8.

12 CLINICAL PHARMACOLOGY

12.1 Mechanism of Action

Elranatamab-bcmm is a bispecific B-cell maturation antigen (BCMA)-directed T-cell engaging antibody that binds BCMA on plasma cells, plasmablasts, and multiple myeloma cells and CD3 on T-cells leading to cytolysis of the BCMA-expressing cells. Elranatamab-bcmm activated T-cells, caused proinflammatory cytokine release, and resulted in multiple myeloma cell lysis.

12.2 Pharmacodynamics

Cytokine Concentrations

Transient elevation of circulating cytokines IL-2, IL-6, IL-8, IL-10, TNF-α, and IFN-γ was observed at dosage levels of 30 µg/kg (0.03 times the approved recommended dosage) and above. After administration of the approved recommended dosage of ELREXFIO, the highest elevation of cytokines was generally observed within 72 hours after first elranatamab-bcmm dose at 12 mg on Day 1, and generally returned to baseline prior to the administration of the first full dose 76 mg on Day 8.

12.3 Pharmacokinetics

Pharmacokinetic parameters are presented as geometric mean (coefficient of variation [CV]%) and are based upon subcutaneously administered unless otherwise specified.

Elranatamab-bcmm exhibits dose proportional pharmacokinetics over dose range from 6 to 76 mg (0.079 to 1 times the approved recommended dosage). Elranatamab-bcmm maximum concentration [33.0 mcg/mL (46%)] is achieved at the end of weekly dosing regimen (i.e., at week 24 of 76 mg weekly dosing). Pharmacokinetic exposures are summarized for the recommended dosage of ELREXFIO in Table 10.

Table 10. Pharmacokinetic Parameters of Elranatamab-bcmm in Subjects with Relapsed or Refractory Multiple Myeloma
Timepoint | Parameters
Timepoint | Cavg; (mcg/mL) | Cmax; (mcg/mL) | Ctrough; (mcg/mL)
First full 76 mg dose | 3.1 (94%) | 3.8 (94%) | 3.3 (102%)
End of weekly dose (week 24) [In patients who have achieved a response.] | 32.0 (46%) | 33.0 (46%) | 30.5 (48%)
Steady state (biweekly dosing) [Steady state exposure of elranatamab biweekly dose is approximated at week 48.] | 17.7 (53%) | 19.5 (51%) | 15.1 (60%)
Steady state (every 4 weeks dosing) [Steady state exposure of elranatamab once every 4 weeks dose is approximated at week 72.] | 8.8 (58%) | 11.5 (54%) | 5.9 (78%)

Absorption

The mean bioavailability of elranatamab-bcmm was 56.2% when administered subcutaneously. The median (min, max) Tmax after elranatamab SC administration was 7 (3 to 7) days.

Distribution

The steady state volume of distribution of elranatamab-bcmm was 7.76 L (33%).

Elimination

The half-life of elranatamab-bcmm is 22 (64%) days at the 76 mg dosage, with clearance of 0.324 L/day (100%) following 24 weeks dosing.

Metabolism

Elranatamab-bcmm is expected to be metabolized into small peptides by catabolic pathways.

Specific Populations

No clinically significant differences in the pharmacokinetics of elranatamab-bcmm were observed based on age (36 to 89 years), sex, race (White, Asian, or Black), body weight (37 to 160 kg), mild or moderate renal impairment (estimated glomerular filtration rate [eGFR] by Modification of Diet in Renal Disease [MDRD] method: 30 to 89 mL/min), or mild hepatic impairment (total bilirubin 1 to ≤1.5 x ULN or any AST greater than ULN).

The effects of severe renal impairment (eGFR 15 to 29 mL/min), end-stage renal disease (eGFR <15 mL/min), or moderate to severe hepatic impairment (total bilirubin >1.5 times ULN and any AST) on the PK of elranatamab-bcmm are unknown.

12.6 Immunogenicity

The observed incidence of anti-drug antibodies is highly dependent on the sensitivity and specificity of the assay. Differences in assay methods preclude meaningful comparisons of the incidence of anti-drug antibodies in the studies described below with the incidence of anti-drug antibodies in other studies, including those of elranatamab-bcmm or of other elranatamab products.

In the MagnetisMM-3 study, of the 168 participant who received recommended step-up and full dosage of ELREXFIO for up to 36 months and are evaluable for presence of ADA against elranatamab-bcmm, 9.5% (16/168) of patients tested positive for anti-elranatamab-bcmm-antibodies. Among the 16 patients who tested positive for ADAs, 56% (9/16) tested positive for neutralizing antibodies against elranatamab-bcmm. The effect of these antibodies on the pharmacokinetics, pharmacodynamics, safety, and/or effectiveness of ELREXFIO products is unknown.

13 NONCLINICAL TOXICOLOGY

13.1 Carcinogenesis, Mutagenesis, Impairment of Fertility

No carcinogenicity or genotoxicity studies have been conducted with elranatamab-bcmm.

No animal studies have been performed to evaluate the effects of elranatamab-bcmm on fertility.

14 CLINICAL STUDIES

14.1 Relapsed or Refractory Multiple Myeloma

The efficacy of ELREXFIO monotherapy was evaluated in patients with relapsed or refractory multiple myeloma in an open-label, single arm, multi-center study (MagnetisMM-3, NCT04649359). The study included patients who were refractory to at least one proteasome inhibitor (PI), one immunomodulatory agent (IMiD), and one anti-CD38 monoclonal antibody. MagnetisMM-3 included 123 patients naïve to prior BCMA-directed therapy (pivotal Cohort A) and 64 patients with prior BCMA-directed antibody drug conjugate (ADC) or chimeric antigen receptor (CAR) T-cell therapy (supportive Cohort B). Patients had measurable disease by International Myeloma Working Group (IMWG) criteria at enrollment. The study included patients with an Eastern Cooperative Oncology Group (ECOG) score of ≤2, adequate baseline bone marrow (absolute neutrophil count ≥1.0 x 10^9/L, platelet count ≥25 x 10^9/L, hemoglobin level ≥8 g/dL), renal (CrCL ≥ 30 mL/min), and hepatic (AST and ALT ≤2.5 x ULN, total bilirubin ≤2 x ULN) function, and left-ventricular ejection fraction ≥40%. Patients with a stem cell transplant within 12 weeks prior to enrollment and active infections were excluded from the study.

Eligible patients received subcutaneous administration of ELREXFIO at step-up doses of 12 mg on Day 1 and 32 mg on Day 4 of treatment, followed by the first treatment dose of ELREXFIO (76 mg) on Day 8 of treatment. Thereafter, patients received 76 mg once weekly. After 24 weeks, in patients who achieved an IMWG response category of partial response or better with responses persisting for at least 2 months, the dose interval was changed from every week to every 2 weeks.

The 123 patients enrolled in pivotal Cohort A had received a median of 5 prior lines of therapy (range: 2 to 22). Ninety-seven patients who were not exposed to prior BCMA-directed therapy and received at least four prior lines of therapy comprised the efficacy population. Among the 97 patients in the efficacy population, the median age was 69 (range: 46 to 89) years with 18.6% of patients ≥75 years of age. Forty percent were female; 59.8% were White, 13.4% were Asian, 7.2% were Hispanic/Latino, 5.2% were Black or African American. Disease stage (R-ISS) at study entry was 20.6% in Stage I, 53.6% in Stage II, and 17.5% in Stage III. The median time since initial diagnosis of multiple myeloma to enrollment was 79.6 (range: 16 to 228) months. 96.9% were triple-class refractory, and 94.8% were refractory to their last line of therapy. 69.1% received prior autologous stem cell transplantation, and 7.2% received prior allogenic stem cell transplantation. High-risk cytogenetics [t(4;14), t(14;16), or del(17p)] were present in 22.7% of patients. 34.0% of patients had extramedullary disease at baseline by BICR.

Efficacy was based on response rate and duration of response (DOR), as assessed by BICR based on IMWG criteria. Efficacy results from BCMA-directed therapy naïve patients are shown in Table 11.

The median (range) time to first response (TTR) was 1.22 (0.9 to 6.5) months. With a median follow-up of 11.1 months (95% CI: 10.6, 12.0) among responders, the DOR rate at 6 months was 90.4% (95% CI: 78.4%, 95.9%) and at 9 months was 82.3% (95% CI: 67.1%, 90.9%).

Table 11. Efficacy Results from BCMA-directed Therapy Naïve Patients
 | N = 97
Objective Response Rate (ORR: sCR+CR+VGPR+PR), n (%) (95% CI) | 56 (57.7%); (47.3, 67.7)
Complete response (CR) or better [Complete response or better = Stringent complete response (sCR) + complete response (CR).] | 25 (25.8%)
Very good partial response (VGPR) | 25 (25.8%)
Partial response (PR) | 6 (6.2%)
Duration of Response (DOR) (months); Median (95% CI) | NR (12.0, NE)
Abbreviations: CI = Confidence interval; NR = Not reached; NE = Not estimable.

Among the 64 patients enrolled in Cohort B who previously received a PI, an IMiD, an anti-CD38 monoclonal antibody, and a BCMA-directed therapy, 63 patients received at least four prior lines of therapy. Patients had received a median of 8 prior lines of therapy (range: 4 to 19); 73% and 32% received prior BCMA-directed ADC and CAR T-cell therapy, respectively.

Confirmed ORR by BICR was 33.3% (95% CI: 22.0, 46.3). After a median (95% CI) follow-up of 10.2 (9.9, 11) months among responders, median DOR was not reached (95% CI: NE, NE) and the DOR rate at 9 months was 84.3% (95% CI: 58.7, 94.7).

16 HOW SUPPLIED/STORAGE AND HANDLING

How Supplied

ELREXFIO® (elranatamab-bcmm) injection is a sterile, preservative-free, clear to slightly opalescent, and colorless to pale brown liquid solution supplied as follows:

- One 76 mg/1.9 mL (40 mg/mL) single-dose vial in a carton. NDC: 0069-4494-02
- One 44 mg/1.1 mL (40 mg/mL) single-dose vial in a carton. NDC: 0069-2522-02

ELREXFIO is supplied in a single-dose glass vial sealed with a rubber stopper (not made of natural rubber latex) and an aluminum seal with a flip-off cap.

Storage and Handling

Store refrigerated at 2 °C to 8 °C (36 °F to 46 °F) in the original carton until time of use to protect from light.

Do not freeze or shake the vial or carton.

17 PATIENT COUNSELING INFORMATION

Advise the patient to read the FDA-approved patient labeling (Medication Guide).

Cytokine Release Syndrome (CRS)

Discuss the signs and symptoms associated with CRS, including fever, hypoxia, chills, hypotension, tachycardia, and elevated liver enzymes. Advise patients to immediately contact their healthcare provider if they experience any signs or symptoms of CRS. Advise patients that they will be hospitalized for 48 hours after administration of the first step-up dose, and for 24 hours after administration of the second step-up dose [see Dosage and Administration (2.5), Warnings and Precautions (5.1)].

Neurologic Toxicity, Including Immune Effector Cell-associated Neurotoxicity Syndrome (ICANS)

Discuss the signs and symptoms associated with neurologic toxicity, including ICANS, including headache, encephalopathy, motor dysfunction, sensory neuropathy, and Guillain-Barré Syndrome. Advise patients to immediately contact their healthcare provider if they experience any signs or symptoms of neurologic toxicity. Advise patients to refrain from driving or operating heavy or potentially dangerous machinery for 48 hours after completing each of the 2 step-up doses and the first treatment dose within the ELREXFIO step-up dosing schedule and in the event of new onset of any neurological toxicity symptoms until symptoms resolve [see Dosage and Administration (2.5), Warnings and Precautions (5.2)].

ELREXFIO REMS

ELREXFIO is available only through a restricted program called ELREXFIO REMS. Inform patients that they will be given an ELREXFIO Patient Wallet Card that they should carry with them at all times and show to all of their healthcare providers. This card describes signs and symptoms of CRS and neurologic toxicity, including ICANS which, if experienced, should prompt the patient to immediately seek medical attention [see Warnings and Precautions (5.3)].

Infections

Discuss the signs and symptoms of infection [see Dosage and Administration (2.5), Warnings and Precautions (5.4)].

Neutropenia

Discuss the signs and symptoms associated with neutropenia and febrile neutropenia [see Dosage and Administration (2.5), Warnings and Precautions (5.5)].

Hepatotoxicity

Advise patients that liver enzyme elevations may occur and that they should report symptoms that may indicate liver toxicity, including fatigue, anorexia, right upper abdominal discomfort, dark urine, or jaundice [see Warnings and Precautions (5.6)].

Embryo-Fetal Toxicity

Advise pregnant women and females of reproductive potential of the potential risk to a fetus. Advise females of reproductive potential to inform their healthcare provider if they are pregnant or become pregnant. Advise females of reproductive potential to use effective contraception during treatment with ELREXFIO and for 4 months after the last dose [see Warnings and Precautions (5.7), Use in Specific Populations (8.1, 8.3)].

Lactation

Advise women not to breastfeed during treatment with ELREXFIO and for 4 months after the last dose [see Use in Specific Populations (8.2)].

Manufactured by:
Pfizer Inc.
NY, NY 10001
US License No. 2001
LAB-1518-4.0

MEDICATION GUIDE

ELREXFIO® (el-reks-fe-o)

(elranatamab-bcmm)
injection, for subcutaneous use

What is the most important information I should know about ELREXFIO?

ELREXFIO may cause serious side effects, including:

- Cytokine Release Syndrome (CRS). CRS is common during treatment with ELREXFIO and can also be serious, life-threatening, or can lead to death. Tell your healthcare provider or get medical help right away if you develop any signs or symptoms of CRS, including:

- fever of 100.4 °F (38 °C) or higher
- trouble breathing
- chills
- dizziness or light-headedness
- fast heartbeat

- headache
- increased liver enzymes in your blood. See “What are the possible side effects of ELREXFIO?” for more information about the signs and symptoms of liver problems.

Due to the risk of CRS, you will receive ELREXFIO on a “step-up dosing schedule” and should be hospitalized for 48 hours after the first “step-up” dose and for 24 hours after the second “step-up” dose of ELREXFIO.
  1. During the step-up dosing schedule:
    - for your first dose, you will receive a smaller “step-up” dose of ELREXFIO on Day 1 of your treatment
    - for your second dose, you will receive a larger “step-up” dose of ELREXFIO, which is usually given on Day 4 of your treatment
    - for your third dose, you will receive the first full “treatment” dose of ELREXFIO, which is usually given on Day 8 of your treatment
  2. If your dose of ELREXFIO is delayed for any reason, you may need to repeat the step-up dosing schedule.
  3. Before each step-up dose and the first full treatment dose of ELREXFIO, you will receive medicines to help reduce your risk of CRS. Your healthcare provider will decide if you need to receive medicines to help reduce your risk of CRS with future doses.
  4. See “How will I receive ELREXFIO?” for more information about how you will receive ELREXFIO.
2. Neurologic problems. ELREXFIO can cause neurologic problems that can be serious or life-threatening. Tell your healthcare provider or get medical help right away if you develop any signs or symptoms of neurologic problems, including:

- headache
- agitation, trouble staying awake, confusion or disorientation, seeing or hearing things that are not real (hallucinations)
- trouble speaking, thinking, remembering things, paying attention, or understanding things

- problems walking, muscle weakness, shaking (tremors), loss of balance, or muscle spasms
- numbness and tingling (feeling like “pins and needles”)
- burning, throbbing, or stabbing pain
- changes in your handwriting

- ELREXFIO is available only through the ELREXFIO Risk Evaluation and Mitigation Strategy (REMS) due to the risk of CRS and neurologic problems. You will receive an ELREXFIO Patient Wallet Card from your healthcare provider. Carry the ELREXFIO Patient Wallet Card with you at all times and show it to all of your healthcare providers. The ELREXFIO Patient Wallet Card lists symptoms of CRS and neurologic problems. Get medical help right away if you develop any of the symptoms listed on the ELREXFIO Patient Wallet Card. You may need to be treated in a hospital.

Your healthcare provider will monitor you for signs and symptoms of CRS and neurologic problems during treatment with ELREXFIO, as well as other side effects, and will treat you if needed. Your healthcare provider may temporarily stop or completely stop your treatment with ELREXFIO if you develop CRS, neurologic problems, or any other side effects that are severe.

If you have any questions about ELREXFIO, ask your healthcare provider.

See “What are possible side effects of ELREXFIO?” for more information about side effects.

What is ELREXFIO?

ELREXFIO is a prescription medicine used to treat adults with multiple myeloma who:

- have already received at least 4 treatment regimens, including a proteasome inhibitor, an immunomodulatory agent and an anti-CD38 monoclonal antibody to treat their multiple myeloma, and
- their cancer has come back or did not respond to prior treatment.

It is not known if ELREXFIO is safe and effective in children.

Before receiving ELREXFIO, tell your healthcare provider about all of your medical conditions, including if you:

- have an infection.
- are pregnant or plan to become pregnant. ELREXFIO may harm your unborn baby.
  Females who are able to become pregnant:
  - Your healthcare provider should do a pregnancy test before you start treatment with ELREXFIO.
  - You should use effective birth control (contraception) during treatment and for 4 months after your last dose of ELREXFIO.
  - Tell your healthcare provider right away if you become pregnant or think that you may be pregnant during treatment with ELREXFIO.
- are breastfeeding or plan to breastfeed. It is not known if ELREXFIO passes into your breast milk. Do not breastfeed during treatment and for 4 months after your last dose of ELREXFIO.

Tell your healthcare provider about all the medicines you take, including prescription and over-the-counter medicines, vitamins, and herbal supplements.

How will I receive ELREXFIO?

- ELREXFIO will be given to you by your healthcare provider as an injection under your skin (subcutaneous injection), usually in your stomach-area (abdomen). Your thigh or another area of your body may also be used.
- See “What is the most important information I should know about ELREXFIO?” for more information about how you will receive ELREXFIO.
- After you receive your first full “treatment” dose, ELREXFIO is usually given 1 time each week through Week 24.
- Starting on Week 25, your future doses will usually be given 1 time every 2 weeks.
- Starting on Week 49, your future doses will usually be given 1 time every 4 weeks.
- Your healthcare provider will decide the time between doses and how long you will receive treatment with ELREXFIO.

If you miss any appointments, call your healthcare provider as soon as possible to reschedule your appointment. It is important for you to be monitored closely for side effects during treatment with ELREXFIO.

What should I avoid while receiving ELREXFIO?

Do not drive, operate heavy or potentially dangerous machinery, or do other dangerous activities during treatment with ELREXFIO:

- for 48 hours after completing each of the 2 doses of ELREXFIO that are part of the “step-up dosing schedule” and your first full treatment dose, and
- at any time during treatment with ELREXFIO if you develop any new neurologic symptoms such as dizziness, confusion, shaking (tremors), sleepiness, or any other symptom that impairs consciousness, until the symptoms go away.

See “What is the most important information I should know about ELREXFIO?” for more information about signs and symptoms of neurologic problems.

What are the possible side effects of ELREXFIO?

ELREXFIO may cause serious side effects, including:

- See “What is the most important information I should know about ELREXFIO?”
- Infections. Upper respiratory tract infections and pneumonia are common during treatment with ELREXFIO. ELREXFIO can cause bacterial and viral infections that are severe, life-threatening, or that may lead to death.
  - Your healthcare provider may prescribe medicines for you to help prevent infections and treat you as needed if you develop an infection during treatment with ELREXFIO.
  - Tell your healthcare provider right away if you develop any signs or symptoms of an infection during treatment with ELREXFIO, including:

- fever of 100.4 °F (38 °C) or higher
- chills
- cough
- shortness of breath

- chest pain
- sore throat
- pain during urination
- feeling weak or generally unwell

- Decreased white blood cell counts. Decreased white blood cell counts are common during treatment with ELREXFIO and can also be severe. Fever can happen with low white blood cell counts and may be a sign that you have an infection. Your healthcare provider will treat you as needed.
- Liver problems. ELREXFIO can cause increased liver enzymes and bilirubin in your blood. These increases can happen with or without you also having CRS. Tell your healthcare provider if you develop any of the following signs or symptoms of liver problems:

- tiredness
- loss of appetite
- pain in your right upper stomach-area (abdomen)

- dark urine
- yellowing of your skin or the white part of your eyes

Your healthcare provider will check your blood and monitor you for signs and symptoms of these serious side effects before you start and during treatment with ELREXFIO and may temporarily or completely stop treatment with ELREXFIO if you develop certain side effects.

The most common side effects of ELREXFIO include:

- tiredness
- injection site reaction, such as redness, itching, pain, bruising, rash, swelling, tenderness
- diarrhea
- muscle and bone pain

- decreased appetite
- rash
- cough
- nausea
- fever

The most common severe abnormal blood test results with ELREXFIO include decreased white blood cells, red blood cells, and platelets.

These are not all of the possible side effects of ELREXFIO.

Call your doctor for medical advice about side effects. You may report side effects to FDA at 1-800-FDA-1088.

General information about the safe and effective use of ELREXFIO.

Medicines are sometimes prescribed for purposes other than those listed in a Medication Guide. You can ask your pharmacist or healthcare provider for more information about ELREXFIO that is written for health professionals.

What are the ingredients in ELREXFIO?

Active ingredient: elranatamab-bcmm

Inactive ingredients: edetate disodium, histidine, L-histidine hydrochloride monohydrate, polysorbate 80, sucrose, and Water for Injection

Manufactured by: Pfizer Inc., NY, NY 10001

US License No. 2001

LAB-1551-3.0

For more information on ELREXFIO, go to www.ELREXFIO.com

For more information on Pfizer, go to www.Pfizer.com or call 1-800-438-1985

This Medication Guide has been approved by the U.S. Food and Drug Administration. Revised: Feb 2026

PRINCIPAL DISPLAY PANEL – 44 mg/1.1 mL Vial

DISPENSE THE ACCOMPANYING
MEDICATION GUIDE TO EACH PATIENT
PROFESSIONAL SAMPLE – NOT FOR SALE

NDC 63539-252-01
Rx only

ELREXFIOTM
(elranatamab-bcmm)
INJECTION
FOR SUBCUTANEOUS USE

44 mg/1.1 mL (40 mg/mL)

One SINGLE-DOSE VIAL

DISCARD UNUSED PORTION.

Pfizer

PRINCIPAL DISPLAY PANEL – 44 mg/1.1 mL Vial Carton

DISPENSE THE ACCOMPANYING
MEDICATION GUIDE TO EACH PATIENT
PROFESSIONAL SAMPLE – NOT FOR SALE

NDC 63539-252-02

ELREXFIOTM
(elranatamab- bcmm)
INJECTION

44 mg/1.1 mL (40 mg/mL)

For Subcutaneous Injection
by a Healthcare Provider Only

One SINGLE-DOSE VIAL

DISCARD UNUSED PORTION.

Rx only

Pfizer
Oncology